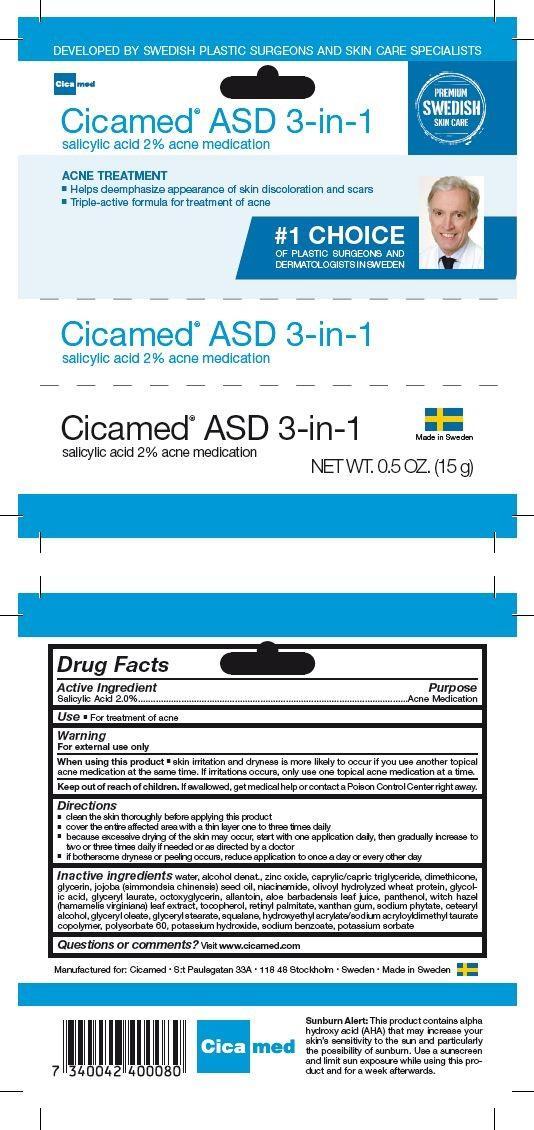 DRUG LABEL: ASD 3-in-1
NDC: 69541-001 | Form: GEL
Manufacturer: Almen Cosmetic Group AB
Category: otc | Type: HUMAN OTC DRUG LABEL
Date: 20150123

ACTIVE INGREDIENTS: SALICYLIC ACID 2 g/100 g
INACTIVE INGREDIENTS: WATER; ALCOHOL; ZINC OXIDE; CAPRYLIC/CAPRIC/LAURIC TRIGLYCERIDE; DIMETHICONE; GLYCERIN; JOJOBA OIL; NIACINAMIDE; OLIVE OIL; HYDROLYZED WHEAT PROTEIN (ENZYMATIC, 3000 MW); GLYCOLIC ACID; GLYCERYL LAURATE; ETHYLHEXYLGLYCERIN; ALLANTOIN; ALOE VERA LEAF; PANTHENOL; WITCH HAZEL; TOCOPHEROL; VITAMIN A PALMITATE; XANTHAN GUM; PHYTATE SODIUM; CETOSTEARYL ALCOHOL; GLYCERYL OLEATE; GLYCERYL MONOSTEARATE; SQUALANE; HYDROXYETHYL ACRYLATE/SODIUM ACRYLOYLDIMETHYL TAURATE COPOLYMER (45000 MPA.S AT 1%); POLYSORBATE 60; POTASSIUM HYDROXIDE; SODIUM BENZOATE; POTASSIUM SORBATE

Active Ingredient Purpose

Salicylic Acid 2.0% .......................................... Acne Medication

Use

for treatment of acne

Keep out of reach of children. If swallowed, get medical help or contact a Poison Control Center right away.

INDICATIONS AND USAGE

Developed by Swedish plastic surgeons and skin care specialists

Cicamed ASD 3-in-1

salicylic acid 2% acne medication

Acne Treatment

- Helps deemphasize appearance of skin discoloration and scars
- Triple-active formula for treatment of acne

#1 choice of plastic surgeons and dermatologists in Sweden

Made in Sweden

Net Wt 0.5 oz. (15g)

Directions

- clean the skin thoroughly before applying this product
- cover the entire affected area with a thin layer one to three times daily
- because excessive drying of the skin may occur, start with one application daily, then gradually increase to two or three times daily if needed or as directed by a doctor
- if bothersome dryness or peeling occurs, reduce application to once a day or every other day

Warnings

For external use only

When using this product

skin irritation and dryness is more likely to occur if you use another topical acne medication at the same time. If irritations occurs, only use one topical acne medication at a time.

Inactive Ingredients

water, alcohol denat., zinc oxide, capylic/capric trigylceride, dimethicone, glycerin, jojoba (simmondsia chinensis) seed oil, niacinamide, olivoyl hydrolyzed wheat protein, glycolic acid, glyceryl laurate, octoxyglycerin, allantoin, aloe barbadensis leaf juice, panthenol, witch hazel (hamamelis virginiana) leaf extract, tocopherol, retinyl palmitate, xanthan gum, sodium phytate, cetearyl alcohol, glyceryl oleate, glyceryl stearate, squalane, hydroxyethyl acrylate/sodium acryloyldimethyl taurate copolymer, polysorbate 60, potassium hydroxide, sodium benzoate, potassium sorbate